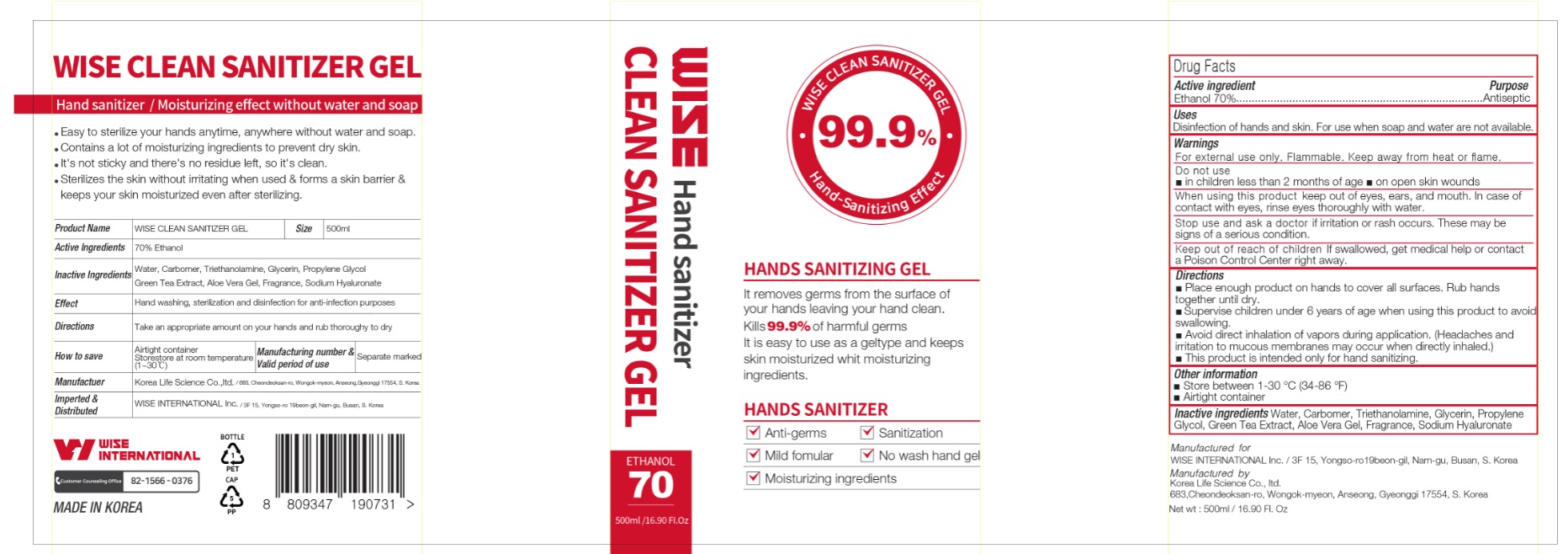 DRUG LABEL: WISE CLEAN SANITIZER Gel
NDC: 77045-570 | Form: GEL
Manufacturer: WISE INTERNATIONAL Inc.
Category: otc | Type: HUMAN OTC DRUG LABEL
Date: 20200506

ACTIVE INGREDIENTS: ALCOHOL 350 mL/500 mL
INACTIVE INGREDIENTS: PROPYLENE GLYCOL; GLYCERIN; HYALURONATE SODIUM; ALOE VERA LEAF; CARBOMER HOMOPOLYMER, UNSPECIFIED TYPE; WATER; TROLAMINE; GREEN TEA LEAF

[WISE CLEAN SANITIZER GEL] 1 * 500 ml : 77045-570-01